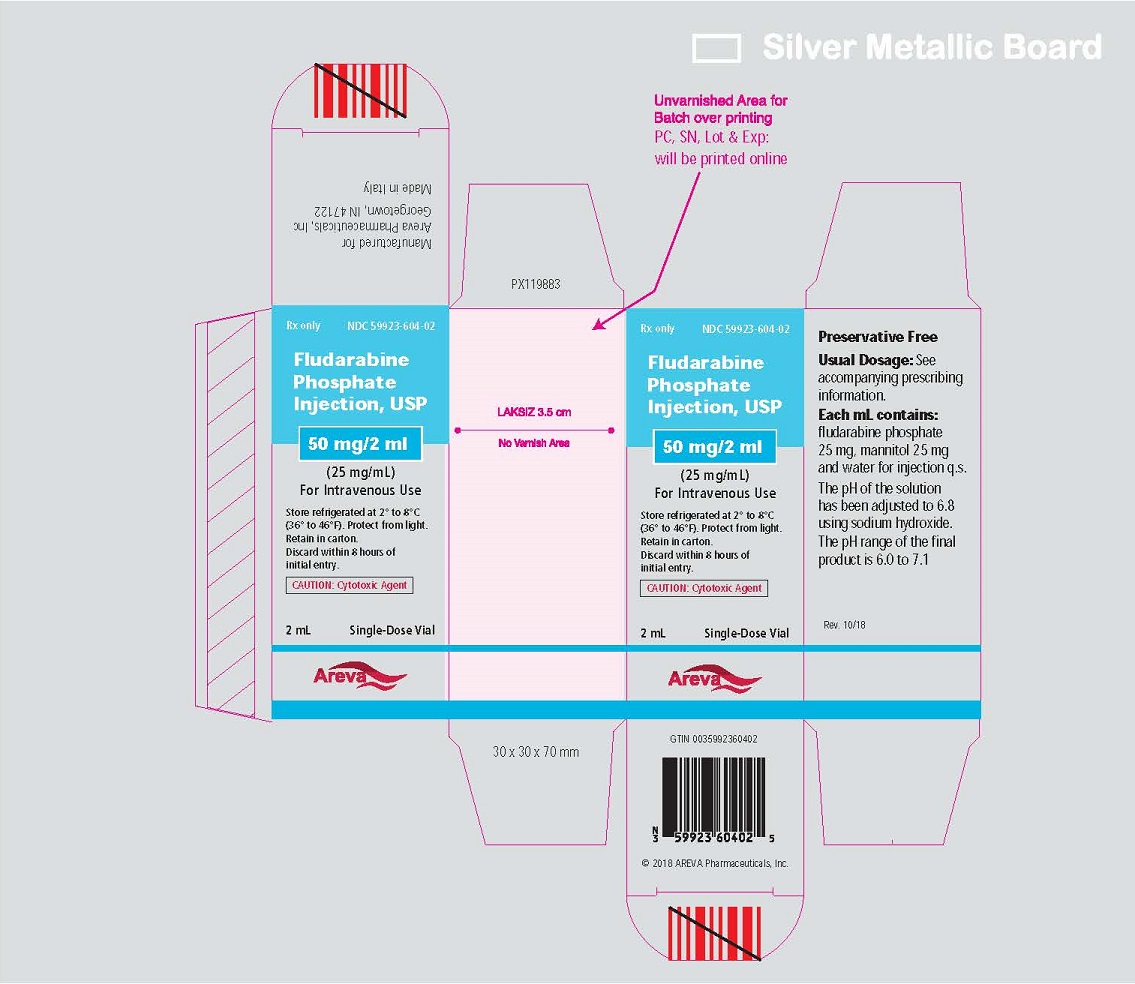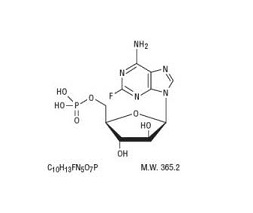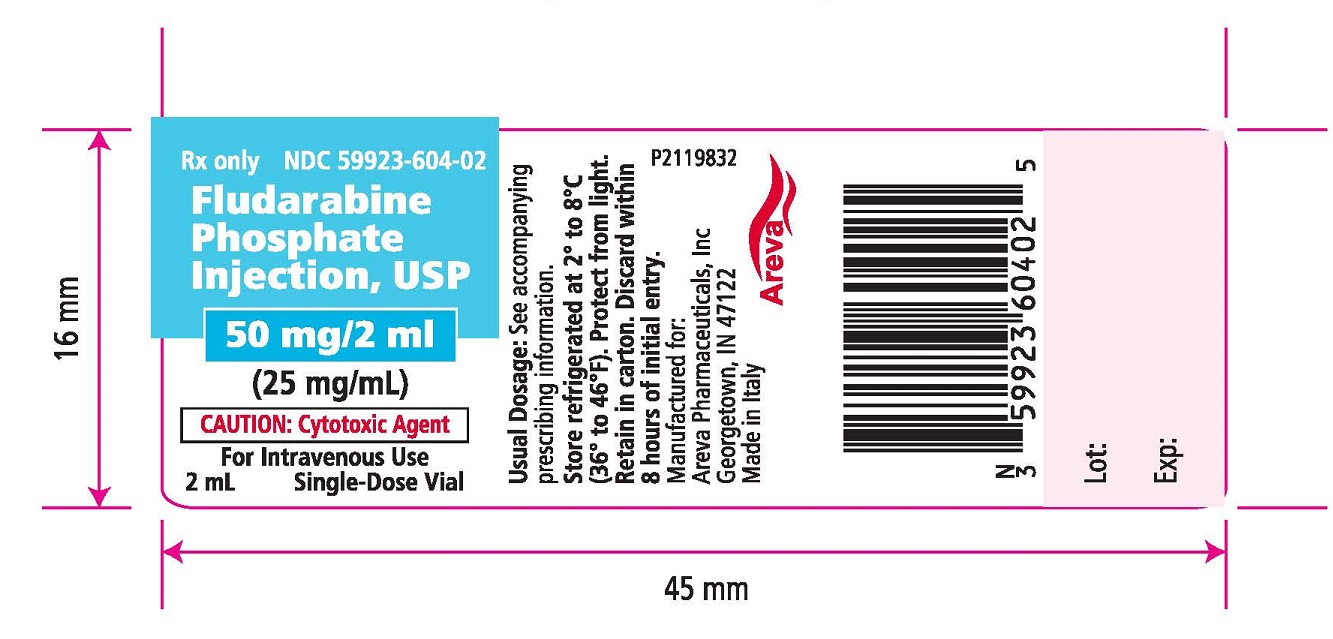 DRUG LABEL: Fludarabine Phosphate
NDC: 59923-604 | Form: INJECTION
Manufacturer: Areva Pharmaceuticals
Category: prescription | Type: HUMAN PRESCRIPTION DRUG LABEL
Date: 20230214

ACTIVE INGREDIENTS: FLUDARABINE PHOSPHATE 25 mg/1 mL
INACTIVE INGREDIENTS: SODIUM HYDROXIDE; MANNITOL; WATER

HIGHLIGHTS OF PRESCRIBING INFORMATION

These highlights do not include all the information needed to use Fludarabine Phosphate safely and effectively. See full prescribing information for Fludarabine Phosphate.
Fludarabine Phosphate Injection, for intravenous use only
Initial U.S. Approval 1991

WARNING: CNS TOXICITY, HEMOLYTIC ANEMIA, AND PULMONARY TOXICITY

See full prescribing information for complete boxed warning.

- Severe central nervous system toxicity occurred in 36% of patients treated with doses approximately four times greater (96 mg/m^2/day for 5 to 7 days) than the recommended dose. This toxicity was seen in ≤0.2% of patients treated at the recommended dose levels (25 m g/m^2). (5.1)
- Instances of life-threatening and sometimes fatal autoimmune hemolytic anemia have been reported after one or more cycle s of treatment. (5.3)
- In a clinical investigation of the combination of fludarabine phosphate with pentostatin (deoxycoformycin) for the treatment of refractory chronic lymphocytic leukemia (CLL), there was an unacceptably high incidence of fatal pulmonary toxicity. (5.5)

1 INDICATIONS AND USAGE

Fludarabine Phosphate Injection is a nucleotide metabolic inhibitor indicated for:

The treatment of adult patients with B-cell chronic lymphocytic leukemia (CLL) who have not responded to or whose disease has progressed during treatment with at least one standard alkylating-agent containing regimen. Benefit in treatment-naïve or non-refractory CLL patients is not established. (1.1)

2 DOSAGE AND ADMINISTRATION

- The recommended adult dose is 25 mg/m^2 administered intravenously over a period of approximately 30 minutes daily for five consecutive days. Each 5 day course of treatment should commence every 28 days. (2.1)
- Reduce dose in patients with creatinine clearance 30 to 70 mL/min/l.73 m^2. Do not use in patients with severe renal impairment (2.2).

3 DOSAGE FORMS AND STRENGTHS

Fludarabine Phosphate Injection is supplied as a 50 mg per 2 mL (25 mg per mL) sterile solution. (3)

4 CONTRAINDICATIONS

- None

5 WARNINGS AND PRECAUTIONS

- Severe bone marrow suppression, notably anemia, thrombocytopenia and neutropenia. Monitor blood counts before and during treatment. (5.2)
- Transfusion-associated graft-versus-host disease. Use only irradiated blood products for transfusions. (5.4)
- Infections. Monitor for infection. (5.2)
- Renal Insufficiency. Reduce dose for moderate renal impairment and monitor closely. Do not administer to patients with severe renal impairment. (5.9)
- Tumor lysis syndrome (TLS). Take precautions for patients at high risk for TLS. (5.8)
- Can cause fetal harm when administered to a pregnant woman. Women should be advised to avoid becoming pregnant. (5.6)

6 ADVERSE REACTIONS

Most common adverse reactions (incidence > 30%) include myelosuppression (neutropenia, thrombocytopenia and anemia), fever, infection, nausea and vomiting, fatigue, anorexia, cough and weakness (6).

To report SUSPECTED ADVERSE REACTIONS, contact Areva at 1-855-853-4760 or FDA at 1-800-FDA-1088 or www.fda.gov/medwatch.

7 DRUG INTREACTIONS

- Fludarabine phosphate injection in combination with pentostatin is not recommended due to the risk of severe pulmonary toxicity (5.5 and 7.1).

8 USE IN SPECIFIC POPULATIONS

- Renal Impairment: Fludarabine Phosphate Injection should not be used in patients with creatinine clearance <30 mL/min/1.73 m^2. For patients with creatinine clearance 30 to 70 mL/min/1.73 m2, reduce the dose (2.2, 5.9, 8.6)

See 17 for PATIENT COUNSELING INFORMATION.

Revised: 10/2018

FULL PRESCRIBING INFORMATION

WARNING: CNS TOXICITY, HEMOLYTIC ANEMIA, AND PULMONARY TOXICITY

WARNING: SEVERE BONE MARROW SUPPRESSION, CNS TOXICITY, HEMOLYTIC ANEMIA, AND PULMONARY TOXICITY

Fludarabine Phosphate Injection should be administered under the supervision of a qualified physician experienced in the use of antineoplastic therapy. Fludarabine phosphate injection can severely suppress bone marrow function. When used at high doses in dose-ranging studies in patients with acute leukemia, fludarabine phosphate was associated with severe neurologic effects, including blindness, coma, and death. This severe central nervous system toxicity occurred in 36% of patients treated with doses approximately four times greater (96 mg/m^2/day for 5 to 7 days) than the recommended dose. Similar severe central nervous system toxicity, including coma, seizures, agitation and confusion, has been reported in patients treated at doses in the range of the dose recommended for chronic lymphocytic leukemia [see Warnings and Precautions (5.2)].

Instances of life-threatening and sometimes fatal autoimmune phenomena such as hemolytic anemia, autoimmune thrombocytopenia/thrombocytopenic purpura (ITP), Evans syndrome, and acquired hemophilia have been reported to occur after one or more cycles of treatment with Fludarabine Phosphate Injection. Patients undergoing treatment with Fludarabine Phosphate Injection should be evaluated and closely monitored for hemolysis [see Warnings and Precautions (5.3)].

In a clinical investigation using fludarabine phosphate in combination with pentostatin (deoxycoformycin) for the treatment of refractory chronic lymphocytic leukemia (CLL), there was an unacceptably high incidence of fatal pulmonary toxicity. Therefore, the use of Fludarabine Phosphate Injection in combination with pentostatin is not recommended [see Warnings and Precautions (5.5)].

1 INDICATIONS AND USAGE

1.1 Indication

Fludarabine Phosphate Injection is indicated for the treatment of adult patients with B-cell chronic lymphocytic leukemia (CLL) who have not responded to or whose disease has progressed during treatment with at least one standard alkylating-agent containing regimen. The safety and effectiveness of Fludarabine Phosphate Injection in previously untreated or non-refractory patients with CLL have not been established.

2 DOSAGE AND ADMINISTRATION

2.1 Recommended Dose

The recommended adult dose of fludarabine phosphate injection is 25 mg/m^2 administered intravenously over a period of approximately 30 minutes daily for five consecutive days. Each 5-day course of treatment should commence every 28 days. Dosage may be decreased or delayed based on evidence of hematologic or nonhematologic toxicity. Physicians should consider delaying or discontinuing the drug if neurotoxicity occurs.

A number of clinical settings may predispose to increased toxicity from Fludarabine Phosphate Injection. These include advanced age, renal impairment, and bone marrow impairment. Such patients should be monitored closely for excessive toxicity and the dose modified accordingly.

The optimal duration of treatment has not been clearly established. It is recommended that three additional cycles of Fludarabine Phosphate Injection be administered following the achievement of a maximal response and then the drug should be discontinued.

2.2 Renal Impairment

Adjustments to the starting dose are recommended to provide appropriate drug exposure in patients with creatinine clearance 30 to 79 mL/min, as estimated by the Cockroft-Gault equations. These adjustments are based on a pharmacokinetic study in patients with renal impairment. Fludarabine Phosphate Injection should not be administered to patients with creatinine clearance less than 30 mL/min.

Starting Dose Adjustment for Renal Impairment

Creatinine Clearance | Starting Dose
≥ 80 mL/min | 25 mg/m^2 (full dose)
50 to 79 mL/min | 20 mg/m^2
30 to 49 mL/min | 15 mg/m^2
< 30 mL/min | Do not administer

Renally impaired patients should be monitored closely for excessive toxicity and the dose modified accordingly.

2.3 Use of Infusion Solutions

Fludarabine Phosphate Injection contains no antimicrobial preservative and should be used within 8 hours of opening. Care must be taken to assure sterility of infusion solutions. Parenteral drug products should be inspected visually for particulate matter and discoloration prior to administration, whenever solution and container permit.

Fludarabine Phosphate Injection should not be mixed with other drugs.

3 DOSAGE FORMS AND STRENGTHS

Fludarabine Phosphate Injection is supplied as a 50 mg per 2 mL (25 mg per mL) sterile solution.

4 CONTRAINDICATIONS

None

5 WARNINGS AND PRECAUTIONS

(see BOXED WARNINGS)

5.1 Dose Dependent Neurologic Toxicities

There are clear dose dependent toxic effects seen with fludarabine phosphate. Dose levels approximately 4 times greater (96 mg/m^2/day for 5 to 7 days) than that recommended for CLL (25 mg/m^2/day for 5 days) were associated with a syndrome characterized by delayed blindness, coma and death. Symptoms appeared from 21 to 60 days following the last dose. Thirteen of 36 patients (36%) who received fludarabine phosphate at high doses (96 mg/m^2/day for 5 to 7 days) developed this severe neurotoxicity. Similar severe central nervous system toxicity, including coma, seizures, agitation and confusion, has been reported in patients treated at doses in the range of the dose recommended for chronic lymphocytic leukemia.

In post-marketing experience neurotoxicity has been reported to occur either earlier or later than in clinical trials (range 7 to 225 days).

The effect of chronic administration of fludarabine phosphate on the central nervous system is unknown; however, patients have received the recommended dose for up to 15 courses of therapy.

Fludarabine phosphate may reduce the ability to drive or use mechanical equipment, since fatigue, weakness, visual disturbances, confusion, agitation and seizures have been observed.

5.2 Bone Marrow Suppression

Severe bone marrow suppression, notably anemia, thrombocytopenia and neutropenia, has been reported in patients treated with fludarabine phosphate. In a Phase I study in adult solid tumor patients, the median time to nadir counts was 13 days (range, 3 to 25 days) for granulocytes and 16 days (range, 2 to 32 days) for platelets. Most patients had hematologic impairment at baseline either as a result of disease or as a result of prior myelosuppressive therapy. Cumulative myelosuppression may be seen. While chemotherapy-induced myelosuppression is often reversible, administration of Fludarabine Phosphate Injection requires careful hematologic monitoring.

Several instances of trilineage bone marrow hypoplasia or aplasia resulting in pancytopenia, sometimes resulting in death, have been reported in adult patients. The duration of clinically significant cytopenia in the reported cases has ranged from approximately 2 months to approximately 1 year. These episodes have occurred both in previously treated or untreated patients.

5.3 Autoimmune Reactions

Instances of life-threatening and sometimes fatal autoimmune phenomena such as hemolytic anemia, autoimmune thrombocytopenia/thrombocytopenic purpura (ITP), Evans syndrome, and acquired hemophilia have been reported to occur after one or more cycles of treatment with fludarabine phosphate in patients with or without a previous history of autoimmune hemolytic anemia or a positive Coombs' test and who may or may not be in remission from their disease. Steroids may or may not be effective in controlling these hemolytic episodes. The majority of patients rechallenged with fludarabine phosphate developed a recurrence in the hemolytic process. The mechanism(s) which predispose patients to the development of this complication has not been identified. Patients undergoing treatment with Fludarabine Phosphate Injection should be evaluated and closely monitored for hemolysis. Discontinuation of therapy with Fludarabine Phosphate Injection is recommended in case of hemolysis.

5.4 Transfusion Associated Graft-Versus-Host Disease

Transfusion-associated graft-versus-host disease has been observed after transfusion of non-irradiated blood in fludarabine phosphate treated patients. Fatal outcome as a consequence of this disease has been reported. Therefore, to minimize the risk of transfusion-associated graft-versus-host disease, patients who require blood transfusion and who are undergoing, or who have received, treatment with Fludarabine Phosphate Injection should receive irradiated blood only.

5.5 Pulmonary Toxicity

In a clinical investigation using fludarabine phosphate in combination with pentostatin (deoxycoformycin) for the treatment of refractory chronic lymphocytic leukemia (CLL) in adults, there was an unacceptably high incidence of fatal pulmonary toxicity. Therefore, the use of Fludarabine Phosphate Injection in combination with pentostatin is not recommended.

5.6 Pregnancy

Based on its mechanism of action, fludarabine phosphate can cause fetal harm when administered to a pregnant woman. There are no adequate and well-controlled studies of Fludarabine Phosphate Injection in pregnant women. Fludarabine phosphate was embryolethal and teratogenic in rats and rabbits. If this drug is used during pregnancy, or if the patient becomes pregnant while taking this drug, the patient should be apprised of the potential hazard to the fetus. Women of childbearing potential should be advised to avoid becoming pregnant [see Use in Specific Populations (8.1)].

5.7 Male Fertility and Reproductive Outcomes

Males with female sexual partners of childbearing potential should use contraception during and after cessation of fludarabine phosphate therapy. Fludarabine phosphate may damage testicular tissue and spermatozoa. Possible sperm DNA damage raises concerns about loss of fertility and genetic abnormalities in fetuses. The duration of this effect is uncertain [see Nonclinical Toxicology (13.1)].

5.8 Tumor Lysis

Tumor lysis syndrome has been associated with fludarabine phosphate treatment. This syndrome has been reported in CLL patients with large tumor burdens. Since fludarabine phosphate can induce a response as early as the first week of treatment, precautions should be taken in those patients at risk of developing this complication.

5.9 Renal Impairment

Fludarabine Phosphate Injection must be administered cautiously in patients with renal impairment. The total body clearance of 2-fluoro-ara-A has been shown to be directly correlated with creatinine clearance. Patients with creatinine clearance 30 to 79 mL/min should have their fludarabine phosphate dose reduced and be monitored closely for excessive toxicity. Fludarabine phosphate should not be administered to patients with creatinine clearance less than 30 mL/min [see Dosage and Administration (2.2) and Use in Specific Populations (8.6)].

In patients aged 65 years or older, creatinine clearance should be measured before start of treatment.

5.10 Vaccination

During and after treatment with Fludarabine Phosphate Injection, vaccination with live vaccines should be avoided.

6 ADVERSE REACTIONS

Because clinical trials are conducted under widely varying conditions, adverse reaction rates observed in the clinical trials of a drug cannot be directly compared to rates in the clinical trials of another drug and may not reflect the rates observed in practice. Very common adverse reactions include myelosuppression (neutropenia, thrombocytopenia and anemia), fever and chills, fatigue, weakness, infection, pneumonia, cough, nausea, vomiting and diarrhea. Other commonly reported events include malaise, mucositis, and anorexia. Serious opportunistic infections have occurred in CLL patients treated with fludarabine phosphate. The most frequently reported adverse reactions and those reactions which are more clearly related to the drug are arranged below according to body system.

6.1 Hematopoietic Systems

Hematologic events (neutropenia, thrombocytopenia, and/or anemia) were reported in the majority of CLL patients treated with fludarabine phosphate. During fludarabine phosphate treatment of 133 patients with CLL, the absolute neutrophil count decreased to less than 500/mm^3 in 59% of patients, hemoglobin decreased from pretreatment values by at least 2 grams percent in 60%, and platelet count decreased from pretreatment values by at least 50% in 55%. Myelosuppression may be severe, cumulative, and may affect multiple cell lines. Bone marrow fibrosis occurred in one CLL patient treated with fludarabine phosphate.

Several instances of trilineage bone marrow hypoplasia or aplasia resulting in pancytopenia, sometimes resulting in death, have been reported in post-marketing surveillance. The duration of clinically significant cytopenia in the reported cases has ranged from approximately 2 months to approximately 1 year. These episodes have occurred both in previously treated or untreated patients.

Life-threatening and sometimes fatal autoimmune phenomena such as hemolytic anemias, autoimmune thrombocytopenia/thrombocytopenic purpura (ITP), Evans syndrome, and acquired hemophilia have been reported to occur in patients receiving fludarabine phosphate [see Warnings and Precautions (5.3)]. The majority of patients rechallenged with fludarabine phosphate developed a recurrence in the hemolytic process.

In post-marketing experience, cases of myelodysplastic syndrome and acute myeloid leukemia, mainly associated with prior, concomitant or subsequent treatment with alkylating agents, topoisomerase inhibitors, or irradiation have been reported.

6.2 Infections

Serious and sometimes fatal infections, including opportunistic infections and reactivations of latent viral infections such as VZV (herpes zoster), Epstein-Barr virus and JC virus (progressive multifocal leukoencephalopathy) have been reported in patients treated with fludarabine phosphate.

Rare cases of Epstein-Barr (EBV) associated lymphoproliferative disorders have been reported in patients treated with fludarabine phosphate.

In post-marketing experience, cases of progressive multifocal leukoencephalopathy have been reported. Most cases had a fatal outcome. Many of these cases were confounded by prior and/or concurrent chemotherapy. The time to onset ranged from a few weeks to approximately one year after initiating treatment.

Of the 133 adult CLL patients in the two trials, there were 29 fatalities during study, approximately 50% of which were due to infection.

6.3 Metabolic

Tumor lysis syndrome has been reported in CLL patients treated with fludarabine phosphate. This complication may include hyperuricemia, hyperphosphatemia, hypocalcemia, metabolic acidosis, hyperkalemia, hematuria, urate crystalluria, and renal failure. The onset of this syndrome may be heralded by flank pain and hematuria.

6.4 Nervous System

Objective weakness, agitation, confusion, seizures, visual disturbances, optic neuritis, optic neuropathy, blindness and coma have occurred in CLL patients treated with fludarabine phosphate at the recommended dose. Peripheral neuropathy has been observed in patients treated with fludarabine phosphate and one case of wrist-drop was reported. There have been additional reports of cerebral hemorrhage though the frequency is not known [see Warnings and Precautions (5)].

6.5 Pulmonary System

Pneumonia, a frequent manifestation of infection in CLL patients, occurred in 16%, and 22% of those treated with fludarabine phosphate in the MDAH and SWOG studies, respectively. Pulmonary hypersensitivity reactions to fludarabine phosphate characterized by dyspnea, cough and interstitial pulmonary infiltrate have been observed.

In post-marketing experience, cases of severe pulmonary toxicity have been observed with fludarabine phosphate use which resulted in ARDS, respiratory distress, pulmonary hemorrhage, pulmonary fibrosis, pneumonitis and respiratory failure. After an infectious origin has been excluded, some patients experienced symptom improvement with corticosteroids.

6.6 Gastrointestinal System

Gastrointestinal disturbances such as nausea and vomiting, anorexia, diarrhea, stomatitis, and hemorrhage have been reported in patients treated with fludarabine phosphate. Elevations of pancreatic enzyme levels have also been reported.

6.7 Cardiovascular

Edema has been frequently reported. One patient developed a pericardial effusion possibly related to treatment with fludarabine phosphate. There have been reports of heart failure and arrhythmia. No other severe cardiovascular events were considered to be drug related.

6.8 Genitourinary System

Hemorrhagic cystitis has been reported in patients treated with fludarabine phosphate.

6.9 Skin

Skin toxicity, consisting primarily of skin rashes, has been reported in patients treated with fludarabine phosphate. Erythema multiforme, Steven-Johnson syndrome, toxic epidermal necrolysis and pemphigus have been reported, with fatal outcomes in some cases.

6.10 Neoplasms

Worsening or flare-up of preexisting skin cancer lesions, as well as new onset of skin cancer, has been reported in patients during or after treatment with fludarabine phosphate.

6.11 Hepatobiliary Disorders

Elevations of hepatic enzyme levels have been reported.

6.12 Adverse Reactions from Clinical Trials

Data in Table 1 are derived from the 133 patients with CLL who received fludarabine phosphate in the MDAH and SWOG studies.

TABLE 1: PERCENT OF CLL PATIENTS REPORTING NON-HEMATOLOGIC ADVERSE REACTIONS

ADVERSE REACTIONS | MDAH; (N=101) | SWOG; (N=32)
ANY ADVERSE REACTION | 88% | 91%
BODY AS A WHOLE | 72 | 84
FEVER | 60 | 69
CHILLS | 11 | 19
FATIGUE | 10 | 38
INFECTION | 33 | 44
PAIN | 20 | 22
MALAISE | 8 | 6
DIAPHORESIS | 1 | 13
ALOPECIA | 0 | 3
ANAPHYLAXIS | 1 | 0
HEMORRHAGE | 1 | 0
HYPERGLYCEMIA | 1 | 6
DEHYDRATION | 1 | 0
NEUROLOGICAL | 21 | 69
WEAKNESS | 9 | 65
PARESTHESIA | 4 | 12
HEADACHE | 3 | 0
VISUAL DISTURBANCE | 3 | 15
HEARING LOSS | 2 | 6
SLEEP DISORDER | 1 | 3
DEPRESSION | 1 | 0
CEREBELLAR SYNDROME | 1 | 0
IMPAIRED MENTATION | 1 | 0
PULMONARY | 35 | 69
COUGH | 10 | 44
PNEUMONIA | 16 | 22
DYSPNEA | 9 | 22
SINUSITIS | 5 | 0
PHARYNGITIS | 0 | 9
UPPER RESPIRATORY INFECTION | 2 | 16
ALLERGIC PNEUMONITIS | 0 | 6
EPISTAXIS | 1 | 0
HEMOPTYSIS | 1 | 6
BRONCHITIS | 1 | 0
HYPOXIA | 1 | 0
GASTROINTESTINAL | 46 | 63
NAUSEA/VOMITING | 36 | 31
DIARRHEA | 15 | 13
ANOREXIA | 7 | 34
STOMATITIS | 9 | 0
GI BLEEDING | 3 | 13
ESOPHAGITIS | 3 | 0
MUCOSITIS | 2 | 0
LIVER FAILURE | 1 | 0
ABNORMAL LIVER FUNCTION TEST | 1 | 3
CHOLELITHIASIS | 0 | 3
CONSTIPATION | 1 | 3
DYSPHAGIA | 1 | 0
CUTANEOUS | 17 | 18
RASH | 15 | 15
PRURITUS | 1 | 3
SEBORRHEA | 1 | 0
GENITOURINARY | 12 | 22
DYSURIA | 4 | 3
URINARY INFECTION | 2 | 15
HEMATURIA | 2 | 3
RENAL FAILURE | 1 | 0
ABNORMAL RENAL FUNCTION TEST | 1 | 0
PROTEINURIA | 1 | 0
HESITANCY | 0 | 3
CARDIOVASCULAR | 12 | 38
EDEMA | 8 | 19
ANGINA | 0 | 6
CONGESTIVE HEART FAILURE | 0 | 3
ARRHYTHMIA | 0 | 3
SUPRAVENTRICULAR TACHYCARDIA | 0 | 3
MYOCARDIAL INFARCTION | 0 | 3
DEEP VENOUS THROMBOSIS | 1 | 3
PHLEBITIS | 1 | 3
TRANSIENT ISCHEMIC ATTACK | 1 | 0
ANEURYSM | 1 | 0
CEREBROVASCULAR ACCIDENT | 0 | 3
MUSCULOSKELETAL | 7 | 16
MYALGIA | 4 | 16
OSTEOPOROSIS | 2 | 0
ARTHRALGIA | 1 | 0
TUMOR LYSIS SYNDROME | 1 | 0

More than 3000 adult patients received fludarabine phosphate in studies of other leukemias, lymphomas, and other solid tumors. The spectrum of adverse effects reported in these studies was consistent with the data presented above.

7 DRUG INTREACTIONS

7.1 Pentostatin

The use of Fludarabine Phosphate Injection in combination with pentostatin is not recommended due to the risk of fatal pulmonary toxicity [see Warnings and Precautions (5.5)].

8 USE IN SPECIFIC POPULATIONS

8.1 Pregnancy

[See Warnings and Precautions (5.6)].

Based on its mechanism of action, fludarabine phosphate can cause fetal harm when administered to a pregnant woman. There are no adequate and well-controlled studies of Fludarabine Phosphate Injection in pregnant women. In rats, repeated intravenous doses of fludarabine phosphate at 2.4 times and 7.2 times the recommended human intravenous dose (25 mg/m^2) administered during organogenesis caused an increase in resorptions, skeletal and visceral malformations (cleft palate, exencephaly, and fetal vertebrae deformities) and decreased fetal body weights. Maternal toxicity was not apparent at 2.4 times the human intravenous dose, and was limited to slight body weight decreases at 7.2 times the human intravenous dose. In rabbits, repeated intravenous doses of fludarabine phosphate at 3.8 times the human intravenous dose administered during organogenesis increased embryo and fetal lethality as indicated by increased resorptions and a decrease in live fetuses. A significant increase in malformations including cleft palate, hydrocephaly, adactyly, brachydactyly, fusions of the digits, diaphragmatic hernia, heart/great vessel defects, and vertebrae/rib anomalies were seen in all dose levels (≥ 0.5 times the human intravenous dose). If this drug is used during pregnancy, or if the patient becomes pregnant while taking this drug, the patient should be apprised of the potential hazard to the fetus. Women of childbearing potential should be advised to avoid becoming pregnant.

8.3 Nursing Mothers

It is not known whether fludarabine phosphate is excreted in human milk. Because many drugs are excreted in human milk and because of the potential for serious adverse reactions including tumorigenicity in nursing infants, a decision should be made to discontinue nursing or discontinue the drug, taking into account the importance of the drug for the mother.

8.4 Pediatric Use

Data submitted to the FDA was insufficient to establish efficacy in any childhood malignancy.

Fludarabine phosphate was evaluated in 62 pediatric patients (median age 10, range 1 to 21) with refractory acute leukemia (45 patients) or solid tumors (17 patients). Limited pharmacokinetic data for fludarabine phosphate are available in children (ages 1 to 21 years). When fludarabine phosphate was administered as a loading dose over 10 minutes immediately followed by a 5-day continuous infusion, steady-state conditions were reached early.

The fludarabine phosphate regimen tested for pediatric lymphocytic leukemia (ALL) patients was a loading bolus of 10.5 mg/m^2/day followed by a continuous infusion of 30.5 mg/m^2/day for 5 days. In 12 pediatric patients with solid tumors, dose-limiting myelosuppression was observed with a loading dose of 8 mg/m^2/day followed by a continuous infusion of 23.5 mg/m^2/day for 5 days. The maximum tolerated dose was a loading dose of 7 mg/m^2/day followed by a continuous infusion of 20 mg/m^2/day for 5 days. Treatment toxicity included bone marrow suppression. Platelet counts appeared to be more sensitive to the effects of fludarabine phosphate than hemoglobin and white blood cell counts. Other adverse events included fever, chills, asthenia, rash, nausea, vomiting, diarrhea, and infection. There were no reported occurrences of peripheral neuropathy or pulmonary hypersensitivity reaction.

8.6 Patients with Renal Impairment

The total body clearance of the principal metabolite 2-fluoro-ara-A correlated with the creatinine clearance, indicating the importance of the renal excretion pathway for the elimination of the drug. Renal clearance represents approximately 40% of the total body clearance. Patients with creatinine clearance 30 to 79 mL/min should have their fludarabine phosphate dose reduced and be monitored closely for excessive toxicity. Due to insufficient data, fludarabine phosphate should not be administered to patients with creatinine clearance less than 30 mL/min [see Dosage and Administration (2.2), Warnings and Precautions (5.9)].

10 OVERDOSAGE

High doses of fludarabine phosphate [see Warnings and Precautions (5)] have been associated with an irreversible central nervous system toxicity characterized by delayed blindness, coma and death. High doses are also associated with severe thrombocytopenia and neutropenia due to bone marrow suppression. There is no known specific antidote for fludarabine phosphate overdosage. Treatment consists of drug discontinuation and supportive therapy.

11 DESCRIPTION

Fludarabine Phosphate Injection contains fludarabine phosphate, a nucleotide metabolic inhibitor. Fludarabine phosphate is a fluorinated nucleotide analog of the antiviral agent vidarabine, 9- ß-D-arabinofuranosyladenine (ara-A), that is relatively resistant to deamination by adenosine deaminase.

The chemical name for fludarabine phosphate is 9H-Purin-6-amine, 2-fluoro-9-(5-0- phosphono- ß-D-arabinofuranosyl)(2-fluoro-ara-AMP). The molecular formula of fludarabine phosphate is C10H13FN5O7P (MW 365.2) and the structure is provided in Figure 1.

Figure 1: Chemical Structure of Fludarabine Phosphate

Each mL contains 25 mg of the active ingredient fludarabine phosphate, 25 mg of mannitol, water for injection, q.s.; and sodium hydroxide to adjust pH to 6.8. The pH range for the final product is 6.0 to 7.1. Fludarabine Phosphate Injection is a sterile solution intended for intravenous administration.

12 CLINICAL PHARMACOLOGY

12 Mechanism of Action

Fludarabine phosphate is rapidly dephosphorylated to 2-fluoro-ara-A and then phosphorylated intracellularly by deoxycytidine kinase to the active triphosphate, 2-fluoro-ara-ATP. This metabolite appears to act by inhibiting DNA polymerase alpha, ribonucleotide reductase and DNA primase, thus inhibiting DNA synthesis. The mechanism of action of this antimetabolite is not completely characterized and may be multi-faceted.

12.3 Pharmacokinetics

Phase I studies in humans have demonstrated that fludarabine phosphate is rapidly converted to the active metabolite, 2-fluoro-ara-A, within minutes after intravenous infusion. Consequently, clinical pharmacology studies have focused on 2-fluoro-ara-A pharmacokinetics. After the five daily doses of 25 mg 2-fluoro-ara-AMP/m2 to cancer patients infused over 30 minutes, 2-fluoro-ara-A concentrations show a moderate accumulation. During a 5-day treatment schedule, 2-fluoroara-A plasma trough levels increased by a factor of about 2. The terminal half-life of 2-fluoro-ara-A was estimated as approximately 20 hours. In vitro, plasma protein binding of fludarabine ranged between 19% and 29%. A correlation was noted between the degree of absolute granulocyte count nadir and increased area under the concentration x time curve (AUC).

13 NONCLINICAL TOXICOLOGY

13.1 Carcinogenesis, Mutagenesis, Impairment of Fertility

No animal carcinogenicity studies with fludarabine have been conducted.

Fludarabine phosphate was clastogenic in vitro to Chinese hamster ovary cells (chromosome aberrations in the presence of metabolic activation) and induced sister chromatid exchanges both with and without metabolic activation. In addition, fludarabine phosphate was clastogenic in vivo (mouse micronucleus assay) but was not mutagenic to germ cells (dominant lethal test in male mice). Fludarabine phosphate was not mutagenic to bacteria (Ames test) or mammalian cells (HGRPT assay in Chinese hamster ovary cells) either in the presence or absence of metabolic activation.

Studies in mice, rats and dogs have demonstrated dose-related adverse effects on the male reproductive system. Observations consisted of a decrease in mean testicular weights in mice and rats with a trend toward decreased testicular weights in dogs and degeneration and necrosis of spermatogenic epithelium of the testes in mice, rats and dogs. The possible adverse effects on fertility in humans have not been adequately evaluated [see Warnings and Precautions (5.7)].

14 CLINICAL STUDIES

14.1 Adults

Two single-arm open-label studies of fludarabine phosphate have been conducted in adult patients with CLL refractory to at least one prior standard alkylating-agent containing regimen. In a study conducted by M.D. Anderson Cancer Center (MDAH), 48 patients were treated with a dose of 22 to 40 mg/m^2 daily for 5 days every 28 days. Another study conducted by the Southwest Oncology Group (SWOG) involved 31 patients treated with a dose of 15 to 25 mg/m^2 daily for 5 days every 28 days. The overall objective response rates were 48% and 32% in the MDAH and SWOG studies, respectively. The complete response rate in both studies was 13%; the partial response rate was 35% in the MDAH study and 19% in the SWOG study. These response rates were obtained using standardized response criteria developed by the National Cancer Institute CLL Working Group and were achieved in heavily pretreated patients. The ability of fludarabine phosphate to induce a significant rate of response in refractory patients suggests minimal cross-resistance with commonly used anti-CLL agents.

The median time to response in the MDAH and SWOG studies was 7 weeks (range of 1 to 68 weeks) and 21 weeks (range of 1 to 53 weeks), respectively. The median duration of disease control was 91 weeks (MDAH) and 65 weeks (SWOG). The median survival of all refractory CLL patients treated with fludarabine phosphate was 43 weeks and 52 weeks in the MDAH and SWOG studies, respectively.

Rai stage improved to Stage II or better in 7 of 12 MDAH responders (58%) and in 5 of 7 SWOG responders (71%) who were Stage III or IV at baseline. In the combined studies, mean hemoglobin concentration improved from 9.0 g/dL at baseline to 11.8 g/dL at the time of response in a subgroup of anemic patients. Similarly, average platelet count improved from 63,500/mm^3 to 103,300/mm^3 at the time of response in a subgroup of patients who were thrombocytopenic at baseline.

15 REFERENCES

1. Preventing Occupational Exposures to Antineoplastic and Other Hazardous Drugs in Health Care Settings. NIOSH Alert 2004-165.
2. OSHA Technical Manual, TED 1-0.l5A, Section VI: Chapter 2. Controlling Occupational Exposure to Hazardous Drugs. OSHA, 1999. http://www.osha.gov/dts/osta/otm/otm_vi/otim_vi_2.html
3. American Society of Health-System Pharmacists. ASHP guidelines on handling hazardous drugs.

Am J Health-Syst Pharm. 2006; 63:172-1193.

1. Polovich, M., White, J. M., & Kelleher, L.O. (eds.) 2005. Chemotherapy and biotherapy guidelines and recommendations for practice (2nd. ed.) Pittsburgh, PA: Oncology Nursing Society

16 HOW SUPPLIED/STORAGE AND HANDLING

16.1 How Supplied

Fludarabine Phosphate Injection, USP is supplied as a sterile solution containing 50 mg/2 mL (25 mg/mL) of fludarabine phosphate in a 2 mL single use vial.

NDC 59923-604-02 one carton containing 1 vial of Fludarabine Phosphate Injection.

16.2 Storage

Store refrigerated between 2° and 8°C (36° and 46°F).

16.3 Handling and Disposal

Procedures for proper handling and disposal should be considered. Consideration should be given to handling and disposal according to guidelines issued for cytotoxic drugs. Several guidelines on this subject have been published.^1-4 Caution should be exercised in the handling and preparation of Fludarabine Phosphate Injection solution. The use of latex gloves and safety glasses is recommended to avoid exposure in case of breakage of the vial or other accidental spillage. If the solution contacts the skin or mucous membranes, wash thoroughly with soap and water; rinse eyes thoroughly with plain water. Avoid exposure by inhalation or by direct contact of the skin or mucous membranes.

17 PATIENT COUNSELING INFORMATION

17.1 Monitoring

Patients should be informed of the importance of periodic assessment of their blood count to detect the development of anemia, neutropenia and thrombocytopenia.

17.2 Laboratory Tests

During treatment, the patient's hematologic profile (particularly neutrophils, red blood cells, and platelets) should be monitored regularly to determine the degree of hematopoietic suppression [see Warnings and Precautions (5.2)].

17.3 Pregnancy

Fludarabine phosphate can cause fetal harm when administered to a pregnant woman. Women should be advised to avoid becoming pregnant [see Warnings and Precautions (5.6)].

Manufactured for:

Areva Pharmaceuticals Inc.

Georgetown, IN 47122

Made in Italy

Revised: October 2018

PACKAGE LABEL PRINCIPAL DISPLAY PANEL

Vial Label

Carton Label